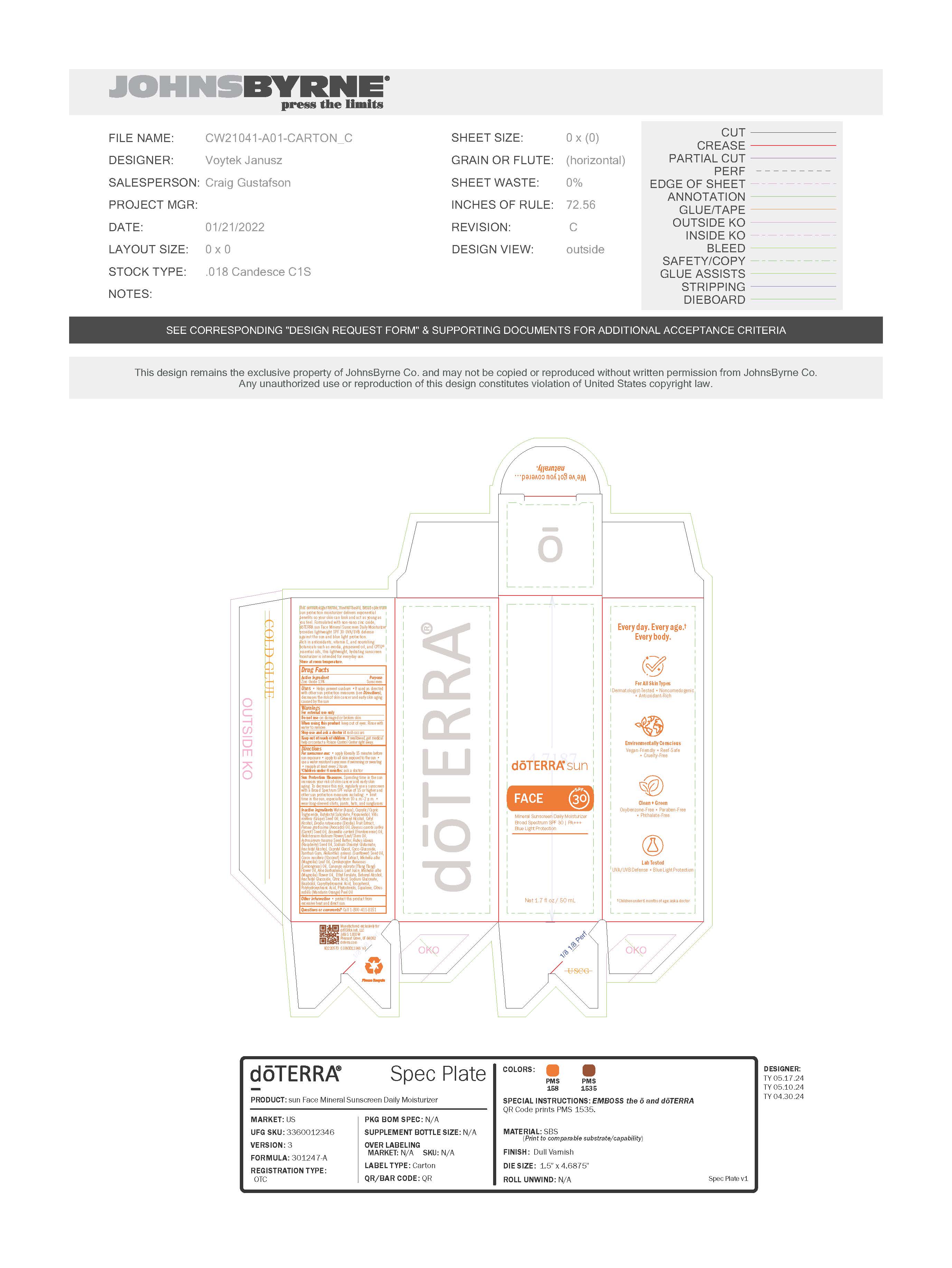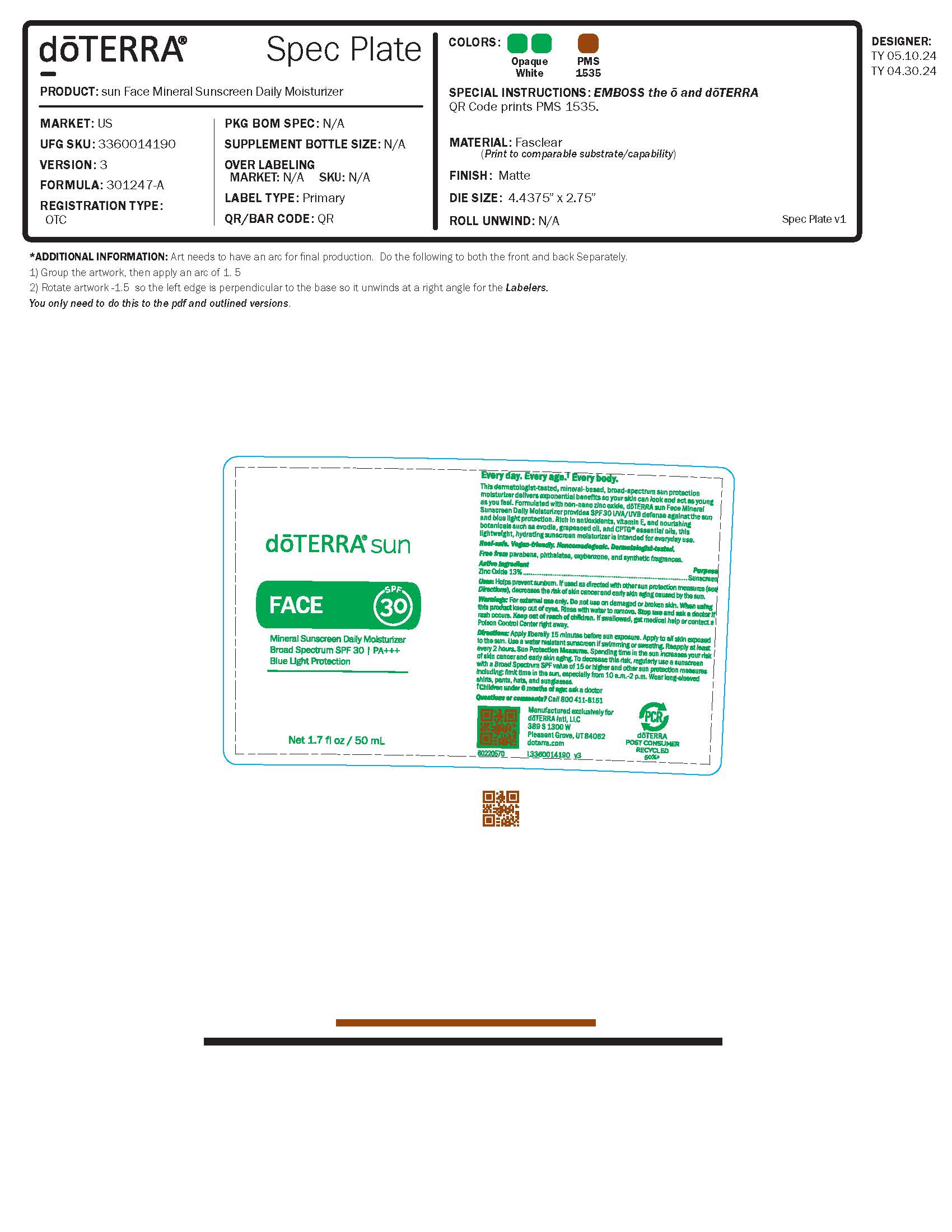 DRUG LABEL: doTERRA sun Face Daily Moisturizer
NDC: 71630-147 | Form: LOTION
Manufacturer: doTERRA International, LLC
Category: otc | Type: HUMAN OTC DRUG LABEL
Date: 20250128

ACTIVE INGREDIENTS: ZINC OXIDE 13 g/100 g
INACTIVE INGREDIENTS: ASTROCARYUM MURUMURU SEED BUTTER; CAPRYLIC/CAPRIC ACID; CITRUS NOBILIS WHOLE; CYMBOPOGON FLEXUOSUS WHOLE; ALOE VERA LEAF; EVODIA RUTAECARPA FRUIT, IMMATURE; MICHELIA ALBA LEAF OIL; POLYHYDROXYSTEARIC ACID (2300 MW); ARACHIDYL ALCOHOL; ARACHIDYL GLUCOSIDE; PROPANEDIOL; BOSWELLIA SERRATA RESIN OIL; ETHYL FERULATE; SUNFLOWER OIL; GLUCOSE PENTAACETATE; RASPBERRY SEED OIL; DODECANEDIOIC ACID; SODIUM GLUCONATE; POTASSIUM SORBATE; CAPRYLYL GLYCOL; SODIUM CHLORIDE; SODIUM BENZOATE; CANANGA ODORATA FLOWER; CARROT SEED OIL; COCOS NUCIFERA WHOLE; MICHELIA ALBA WHOLE; SODIUM STEAROYL GLUTAMATE; GRAPE SEED OIL; .ALPHA.-BISABOLOL, (+)-; COCO GLUCOSIDE; XANTHAN GUM; BUTYLOCTYL SALICYLATE; BUTYLOCTANOL; CITRIC ACID MONOHYDRATE; CETYL ALCOHOL; CAPRYLHYDROXAMIC ACID; TOCOPHEROL; SQUALENE; WATER; AVOCADO OIL; HELICHRYSUM ITALICUM FLOWER OIL

doTERRA Sun Mineral Sunscreen Daily Moisturizer

Active Ingredient Purpose
Zinc Oxide 13%.......................................... Sunscreen

Mineral Sunscreen Daily Moisturizer

This dermatologist-tested, mineral-based, broad-spectrum
sun protection moisturizer delivers exponential
benefits so your skin can look and act as young as
you feel. Formulated with non-nano zinc oxide,
doTERRA sun Face Mineral Sunscreen Daily Moisturizer
provides lightweight SPF 28 UVA/UVB defense
against the sun and blue light protection.
Rich in antioxidants, vitamin E, and nourishing
botanicals such as evodia, grapeseed oil, and CPTG®
essential oils, this lightweight, hydrating sunscreen
moisturizer is intended for everyday use.

INDICATIONS AND USAGE

Helps prevent sunburn •If used as directed
with other sun protection measures (see Directions),
decreases the risk of skin cancer and early skin aging
caused by the sun

WARNINGS

For external use only
Do not use on damaged or broken skin
When using this product keep out of eyes. Rinse with
water to remove.
Stop use and ask a doctor if rash occurs
Keep out of reach of children. If swallowed, get medical
help or contact a Poison Control Center right away.

WHEN USING

For sunscreen use: • apply liberally 15 minutes before
sun exposure • apply to all skin exposed to the sun •
use a water resistant sunscreen if swimming or sweating
• reapply at least every 2 hours
†Children under 6 months: Ask a doctor

OTHER SAFETY INFORMATION

Sun Protection Measures. Spending time in the sun
increases your risk of skin cancer and early skin
aging. To decrease this risk, regularly use a sunscreen
with a Broad Spectrum SPF value of 15 or higher and
other sun protection measures including: • limit
time in the sun, especially from 10 a.m.–2 p.m. •
wear long-sleeved shirts, pants, hats, and sunglasses

Inactive ingredients Water (Aqua), Caprylic/Capric
Triglyceride, Butyloctyl Salicylate, Propanediol, Vitis
vinifera (Grape) Seed Oil, Cetearyl Alcohol, Cetyl
Alcohol, Evodia rutaecarpa (Evodia) Fruit Extract,
Persea gratissima (Avocado) Oil, Daucus carota sativa
(Carrot) Seed Oil, Boswellia carterii (Frankincense) Oil,
Helichrysum italicum Flower/Leaf/Stem Oil,
Astrocaryum tucuma Seed Butter, Rubus idaeus
(Raspberry) Seed Oil, Sodium Stearoyl Glutamate,
Arachidyl Alcohol, Caprylyl Glycol, Coco-Glucoside,
Xanthan Gum, Helianthus annuus (Sunflower) Seed Oil,
Cocos nucifera (Coconut) Fruit Extract, Michelia alba
(Magnolia) Leaf Oil, Cymbopogon flexuosus
(Lemongrass) Oil, Cananga odorata (Ylang Ylang)
Flower Oil, Aloe barbadensis Leaf Juice, Michelia alba
(Magnolia) Flower Oil, Ethyl Ferulate, Behenyl Alcohol,
Arachidyl Glucoside, Citric Acid, Sodium Gluconate,
Bisabolol, Caprylhydroxamic Acid, Tocopherol,
Polyhydroxystearic Acid, Phytosterols, Squalene, Citrus
nobilis (Mandarin Orange) Peel Oil

Other information • protect this product from
excessive heat and direct sun.

Questions or comments? Call 1-800-411-8151

Keep out of reach of children

DOSAGE AND ADMINISTRATION

Apply topically

PACKAGE LABEL

Mineral sunscreen moisturizer

Broad Spectrum SPF 30